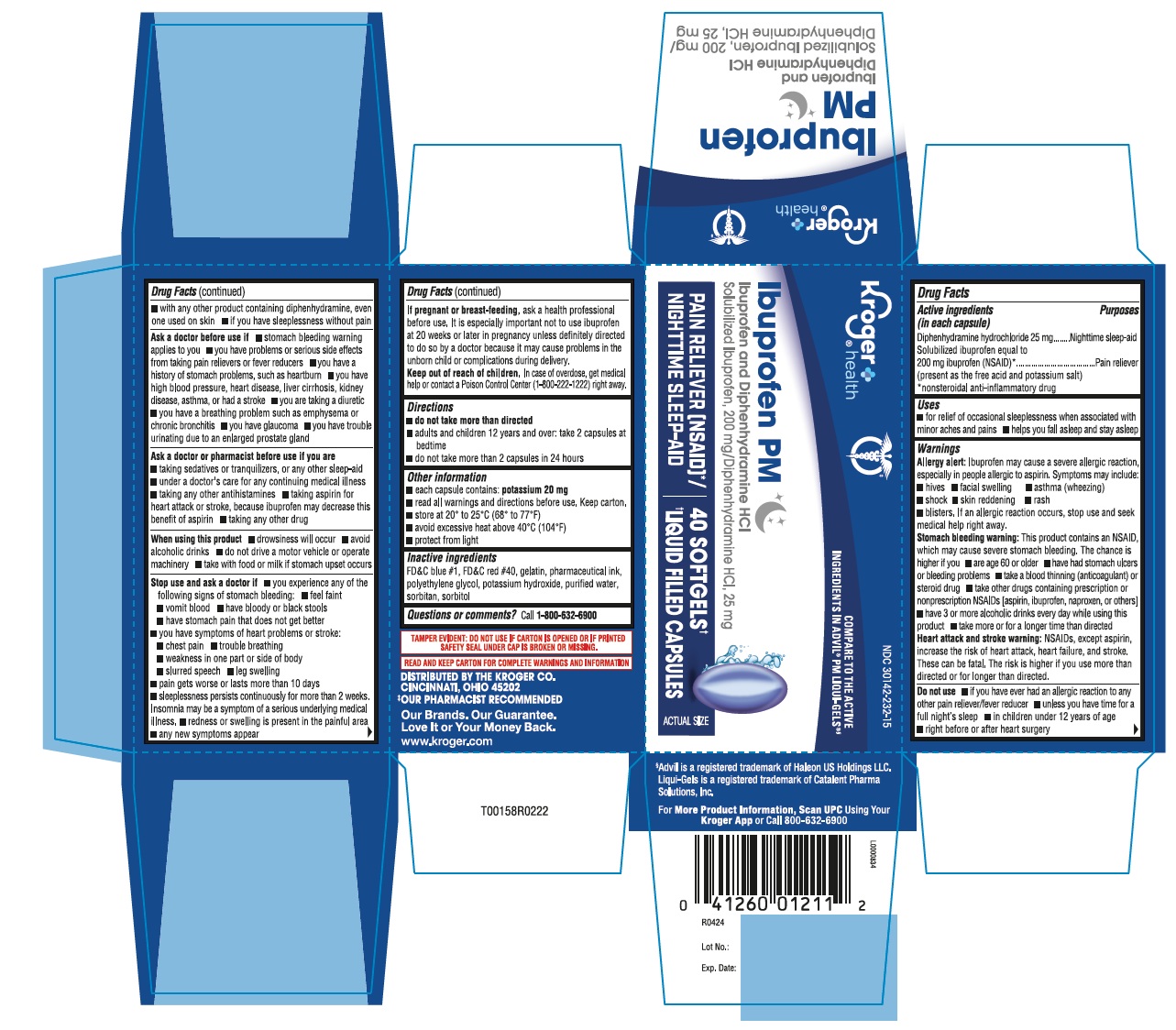 DRUG LABEL: Ibuprofen PM
NDC: 30142-232 | Form: CAPSULE, LIQUID FILLED
Manufacturer: KROGER COMPANY
Category: otc | Type: HUMAN OTC DRUG LABEL
Date: 20251216

ACTIVE INGREDIENTS: IBUPROFEN 200 mg/1 1; DIPHENHYDRAMINE HYDROCHLORIDE 25 mg/1 1
INACTIVE INGREDIENTS: FD&C BLUE NO. 1; FD&C RED NO. 40; GELATIN; POLYETHYLENE GLYCOL, UNSPECIFIED; POTASSIUM HYDROXIDE; WATER; SORBITAN; SORBITOL

Ibuprofen PM capsules

Active ingredients (in each capsule)

Diphenhydramine hydrochloride 25 mg

Solubilized ibuprofen equal to

200 mg ibuprofen (NSAID)*

(present as the free acid and potassium salt)

*nonsteroidal anti-inflammatory drug

Purposes

Nighttime sleep-aid

Pain reliever

Uses

■ for relief of occasional sleeplessness when associated with minor aches and pains

■ helps you fall asleep and stay asleep

Warnings

Allergy alert:Ibuprofen may cause a severe allergic reaction, especially in people allergic to aspirin. Symptoms may include:

■ hives

■ facial swelling

■ asthma (wheezing)

■ shock

■ skin reddening

■ rash

■ blisters.

If an allergic reaction occurs, stop use and seek medical help right away.

Stomach bleeding warning:This product contains an NSAID, which may cause severe stomach bleeding. The chance is higher if you

■ are age 60 or older

■ have had stomach ulcers or bleeding problems

■ take a blood thinning (anticoagulant) or steroid drug

■ take other drugs containing prescription or nonprescription NSAIDs [aspirin, ibuprofen, naproxen, or others]

■ have 3 or more alcoholic drinks every day while using this product

■ take more or for a longer time than directed

Heart attack and stroke warning:NSAIDs, except aspirin, increase the risk of heart attack, heart failure, and stroke. These can be fatal. The risk is higher if you use more than directed or for longer than directed.

Do not use

■ if you have ever had an allergic reaction to any other pain reliever/fever reducer

■ unless you have time for a full night’s sleep

■ in children under 12 years of age

■ right before or after heart surgery

■ with any other product containing diphenhydramine, even one used on skin

■ if you have sleeplessness without pain

Ask a doctor before use if

■ stomach bleeding warning applies to you

■ you have problems or serious side effects from taking pain relievers or fever reducers

■ you have a history of stomach problems, such as heartburn

■ you have high blood pressure, heart disease, liver cirrhosis, kidney disease, asthma, or had a stroke

■ you are taking a diuretic

■ you have a breathing problem such as emphysema or chronic bronchitis

■ you have glaucoma

■ you have trouble urinating due to an enlarged prostate gland

Ask a doctor or pharmacist before use if you are

■ taking sedatives or tranquilizers, or any other sleep-aid

■ under a doctor's care for any continuing medical illness

■ taking any other antihistamines

■ taking aspirin for heart attack or stroke, because ibuprofen may decrease this benefit of aspirin

■ taking any other drug

When using this product

■ drowsiness will occur

■ avoid alcoholic drinks

■ do not drive a motor vehicle or operate machinery

■ take with food or milk if stomach upset occurs

Stop use and ask a doctor if

■ you experience any of the following signs of stomach bleeding:

■ feel faint

■ vomit blood

■ have bloody or black stools

■ have stomach pain that does not get better

■ you have symptoms of heart problems or stroke:

■ chest pain ■ trouble breathing ■ weakness in one part or side of body ■ slurred speech ■ leg swelling

■ pain gets worse or lasts more than 10 days

■ sleeplessness persists continuously for more than 2 weeks. Insomnia may be a symptom of a serious underlying medical illness

■ redness or swelling is present in the painful area

■ any new symptoms appear

If pregnant or breast-feeding,

ask a health professional before use. It is especially important not to use ibuprofen at 20 weeks or later in pregnancy unless definitely directed to do so by a doctor because it may cause delivery problems in the unborn child or complications during delivery.

Keep out of reach of children.

In case of overdose, get medical help or contact a Poison Control Center right away.

Directions

■ do not take more than directed

■ adults and children 12 years and over: take 2 capsules at bedtime

■ do not take more than 2 capsules in 24 hours

Other information

■ each capsule contains: potassium 20 mg

■ read all warnings and directions before use. Keep carton.

■ store at 20° to 25°C (68° to 77°F)

■ avoid excessive heat above 40°C (104°F)

■ protect from light

Inactive ingredients

FD&C blue #1, FD&C red #40, gelatin, pharmaceutical ink, polyethylene glycol, potassium hydroxide, purified water, sorbitan, sorbitol

Questions?

call toll-free 1-800-632-6900

TAMPER EVIDENT: DO NOT USE IF CARTON IS OPENED OR IF

PRINTED SAFETY SEAL UNDER CAP IS BROKEN OR MISSING.

READ AND KEEP CARTON FOR COMPLETE WARNINGS AND INFORMATION

***Advil®PM LIQUI-GELS®is a registered trademark of Haleon US Holdings LLC,

Liquid-Gels is a registered trademark oof Catalent Pharma Solutions, Inc.

DISTRIBUTED BY THE KROGER CO.

CINCINNATI, OHIO 45202

OUR PHARMACIST RECOMMENDED

OUR BRANDS OUR GUARANTEE

LOVE IT OR YOUR MONEY BACK.

WWW.KROGER.COM

FOR MORE PRODUCT INFORMATION, SCAN UPC USING YOUR KROGER APP OR CALL 800-632-6900

L0000834

R0424

Lot No.:

Exp. Date:

40's count carton label

COMPARE TO the active ingredients of
Advil® PM LIQUI-GELS®

Kroger®

health

Ibuprofen PM

Ibuprofen & Diphenhydramine HCl

Solubilized Ibuprofen, 200 mg/ Diphenhydramine HCl, 25 mg

Pain Reliever (NSAID)/
Nighttime Sleep-Aid

actual size

40 SOFTGEL**

CAPSULES

**liquid filled capsules